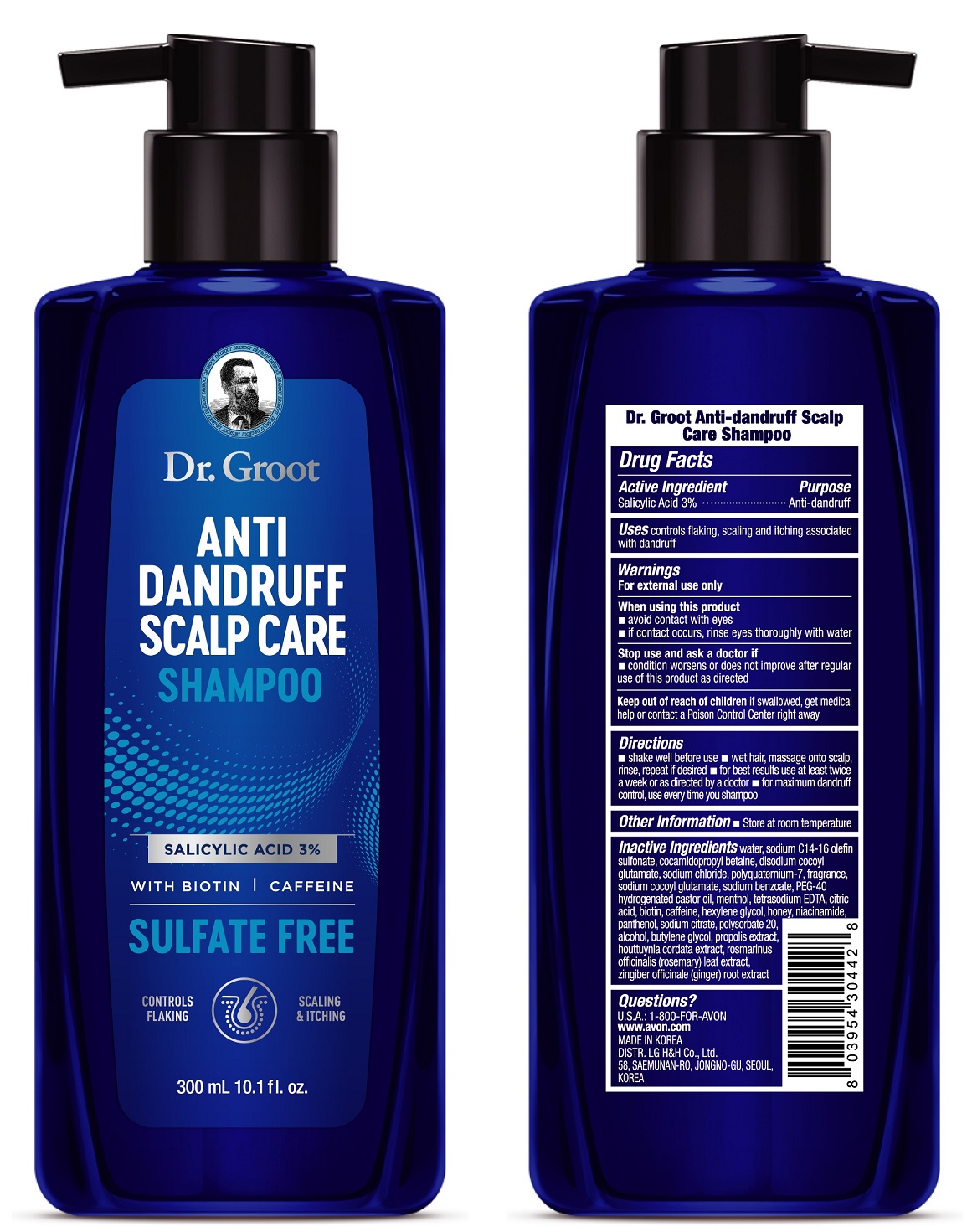 DRUG LABEL: Dr. Groot Anti-dandruff Scalp Care
NDC: 43136-701 | Form: SHAMPOO
Manufacturer: TAI GUK PHARM. CO., LTD
Category: otc | Type: HUMAN OTC DRUG LABEL
Date: 20250101

ACTIVE INGREDIENTS: SALICYLIC ACID 30 mg/1 mL
INACTIVE INGREDIENTS: WATER; SODIUM C14-16 OLEFIN SULFONATE; COCAMIDOPROPYL BETAINE; SODIUM CHLORIDE; DISODIUM COCOYL GLUTAMATE

Dr. Groot Anti-dandruff Scalp Care Shampoo

Drug Facts

Active ingredient

Salicylic Acid 3%

Purposes

Anti-dandruff

Uses

controls flaking, scaling and itcing associated with dandruff

Warnings

For external use only

When using this product

◾ avoid contact with the eyes

◾ if contact occurs, rinse eyes thoroughly with water

Stop use and ask a doctor if

◾condition worsens or does not improve after regular use of this product as directed.

KEEP OUT OF REACH OF CHILDREN

Keep out of reach of childrenif swallowed, get medical help or contact a Poison Control Center right away

Directions

◾ shake well before use ◾ wet hair, massage onto scalp, rinse, repeat if desired ◾ for best results use at least twice a week or as directed by a doctor ◾ for maximum dandruff control, use every time you shampoo

Other information

◾ Store at room temperature

Inactive Ingredients

water, sodium C14-16 olefin sulfonate, cocamidopropyl betaine, disodium cocoyl glutamate, sodium chloride, polyquaternium-7, fragrance, sodium cocoyl glutamate, sodium benzoate, PEG-40 hydrogenated castor oil, menthol, tetrasodium EDTA, citric acid, biotin, caffeine, hexylene glycol, honey, niacinamide, panthenol, sodium citrate, polysorbate 20, alcohol, butylene glycol, propolis extract, houttuynia cordata extract, rosmarinus officinalis (rosemary) leaf extract, zingiber officinale (ginger) root extract

Questions?

U.S.A.: 1-800-FOR-AVON

www.avon.com

MADE IN KOREA

DISTR. LG H&H Co., Ltd.
58, SAEMUNAN-RO, JONGNO-GU,
SEOUL, KOREA

PRINCIPAL DISPLAY PANEL - 300 mL Bottle Carton

Dr. Groot

ANTI
DANDRUFF
SCALP CARE
SHAMPOO

SALICYLIC ACID 3%

WITH BIOTIN | CAFFEINE

SULFATE FREE

CONTROLS FLAKING

SCALING & ITCHING

300 mL 10.1 fl. oz.